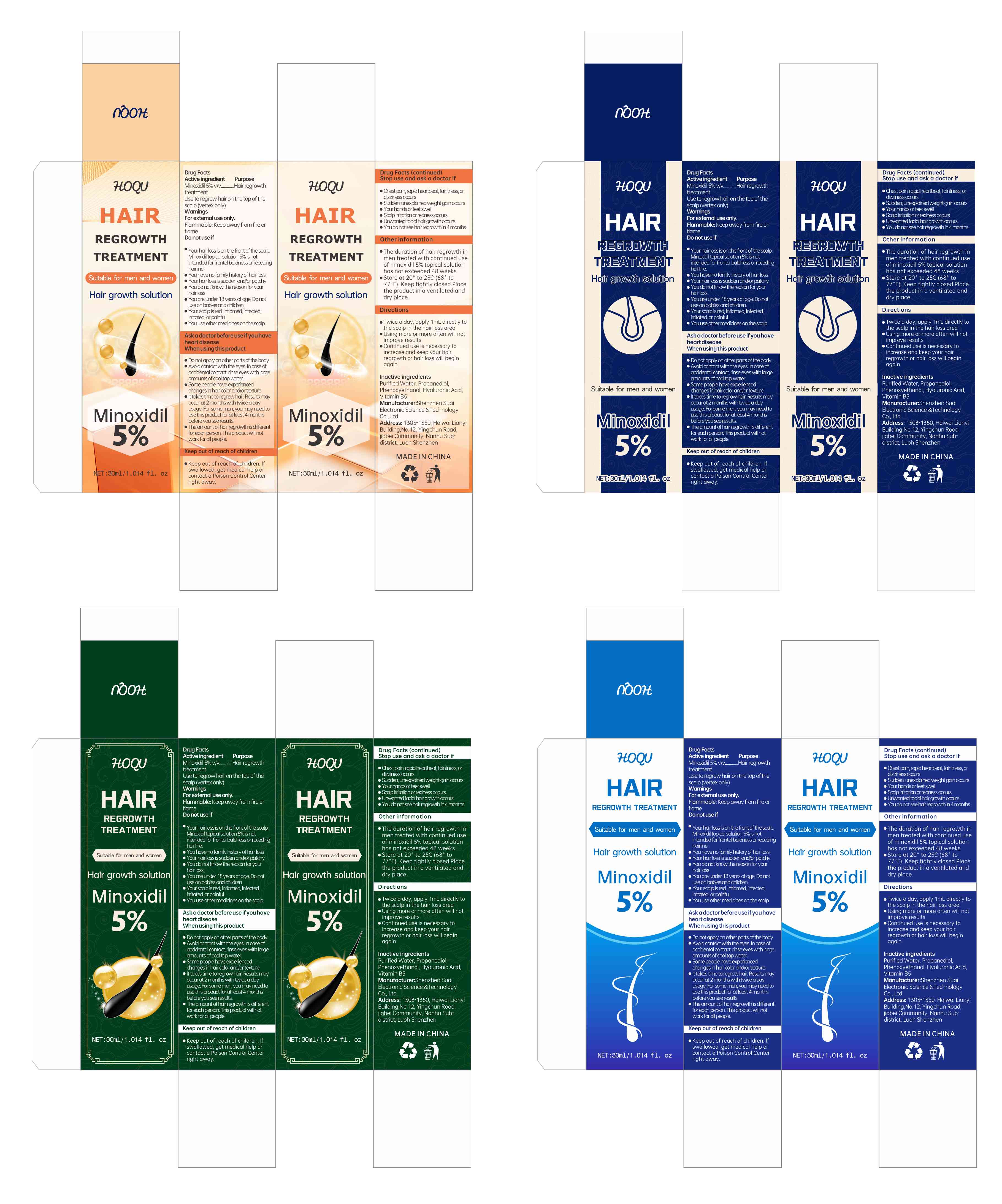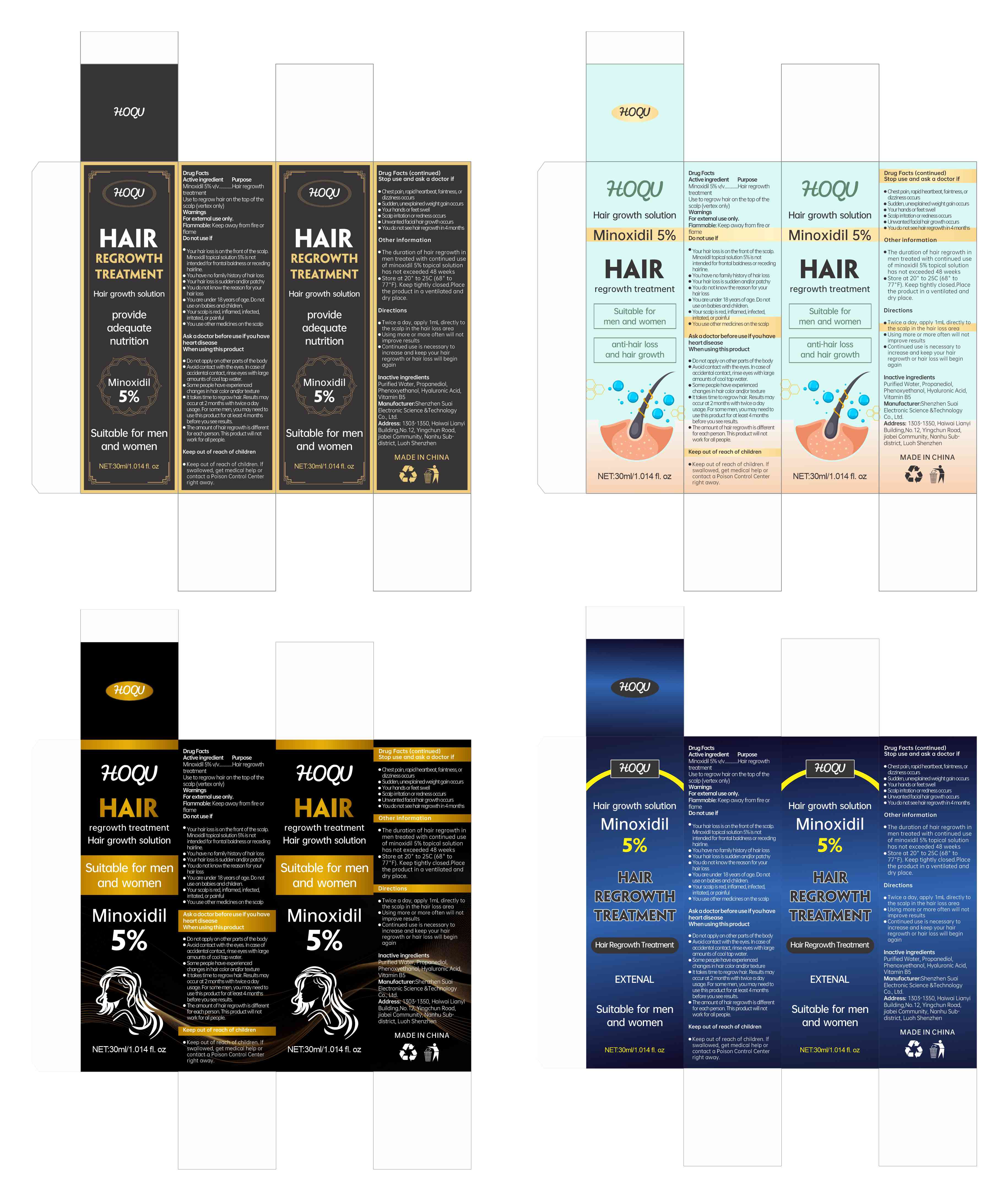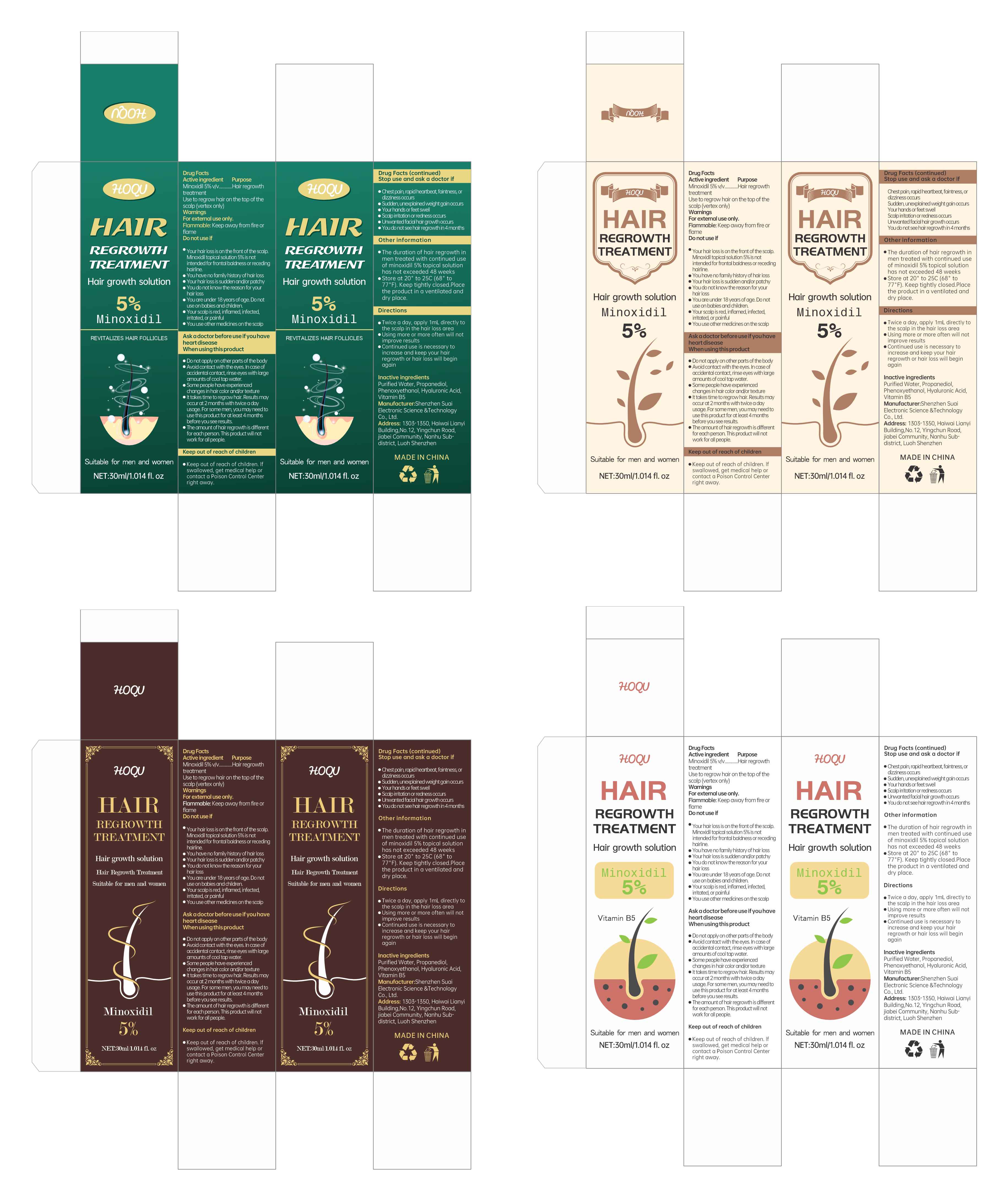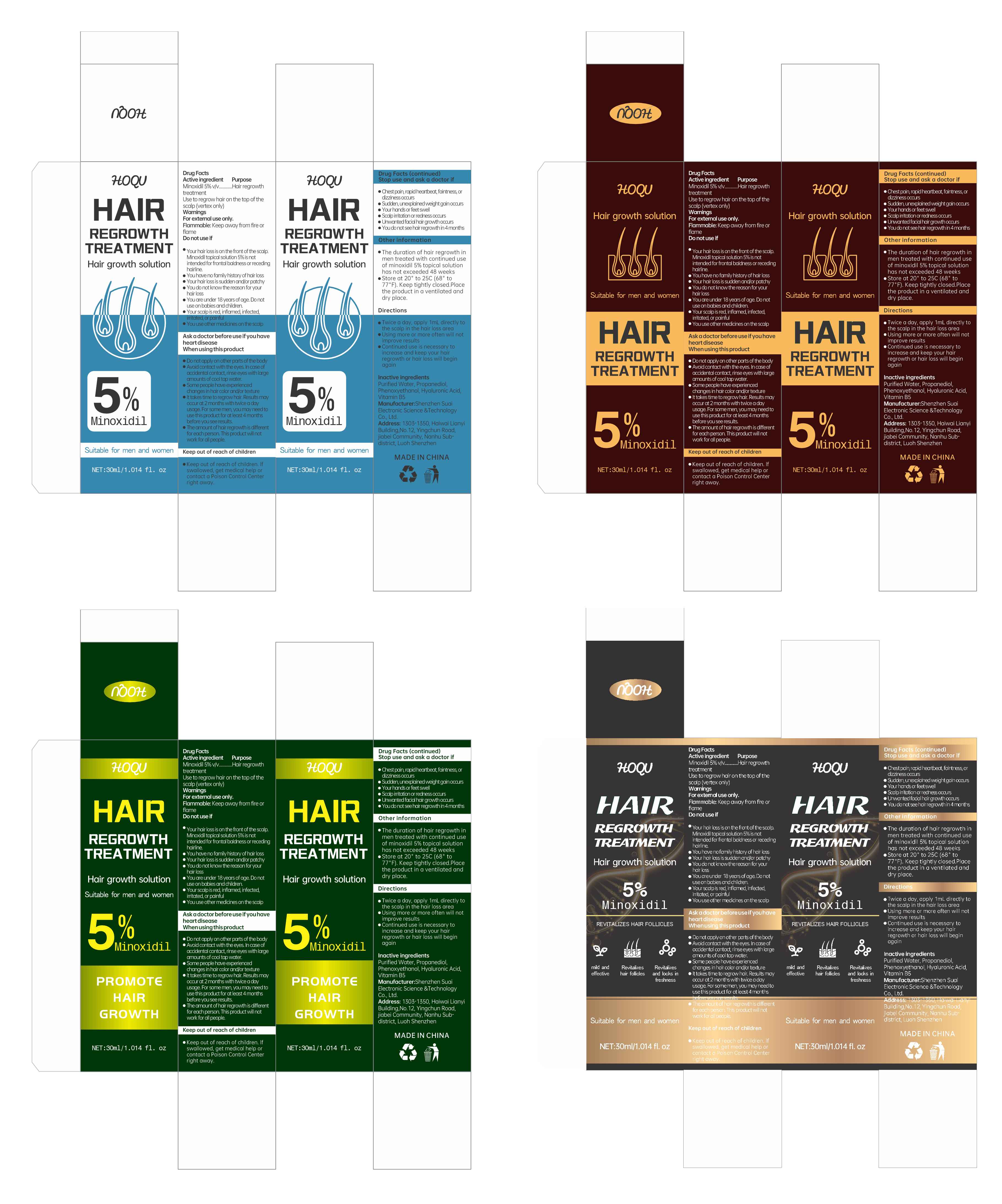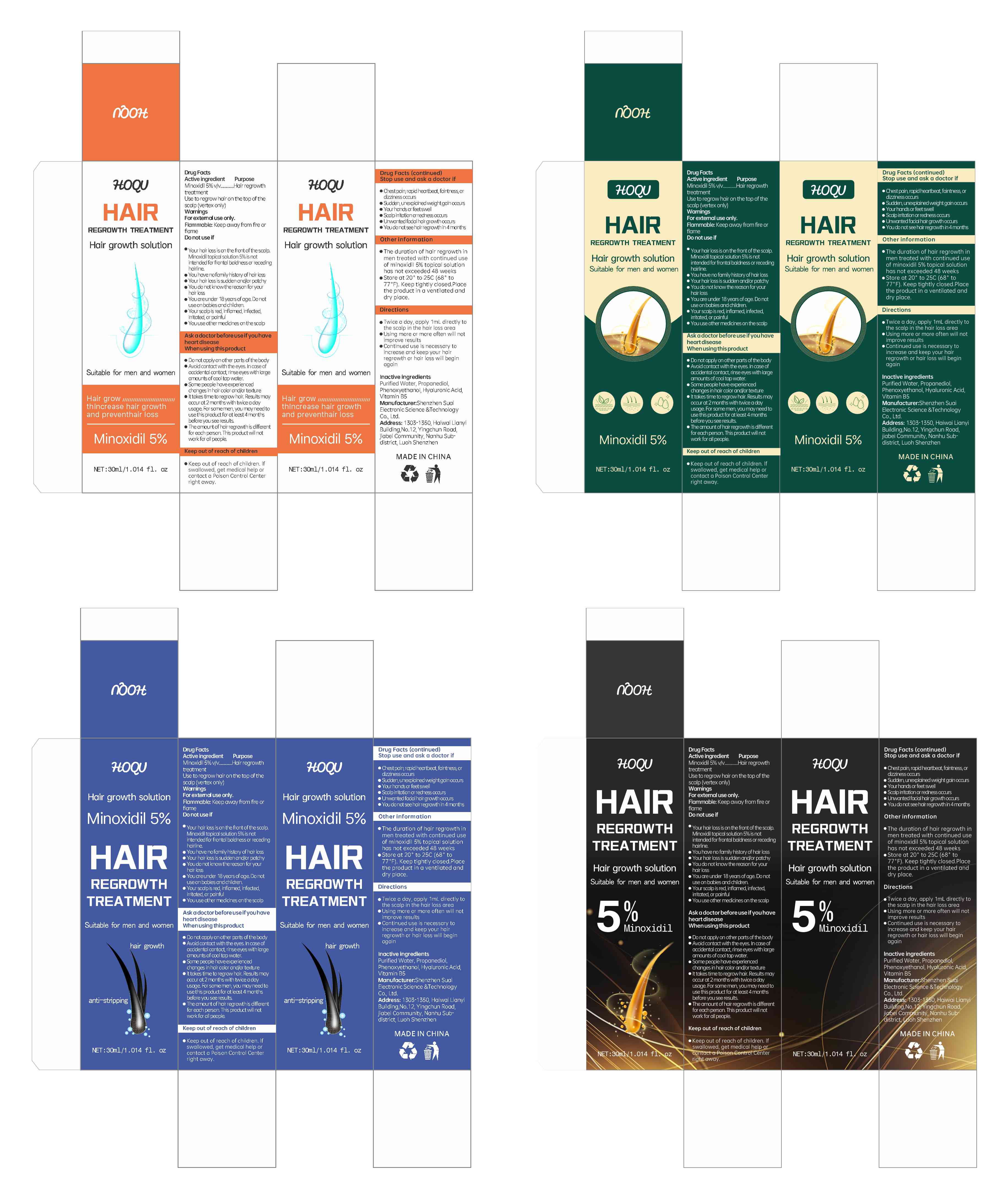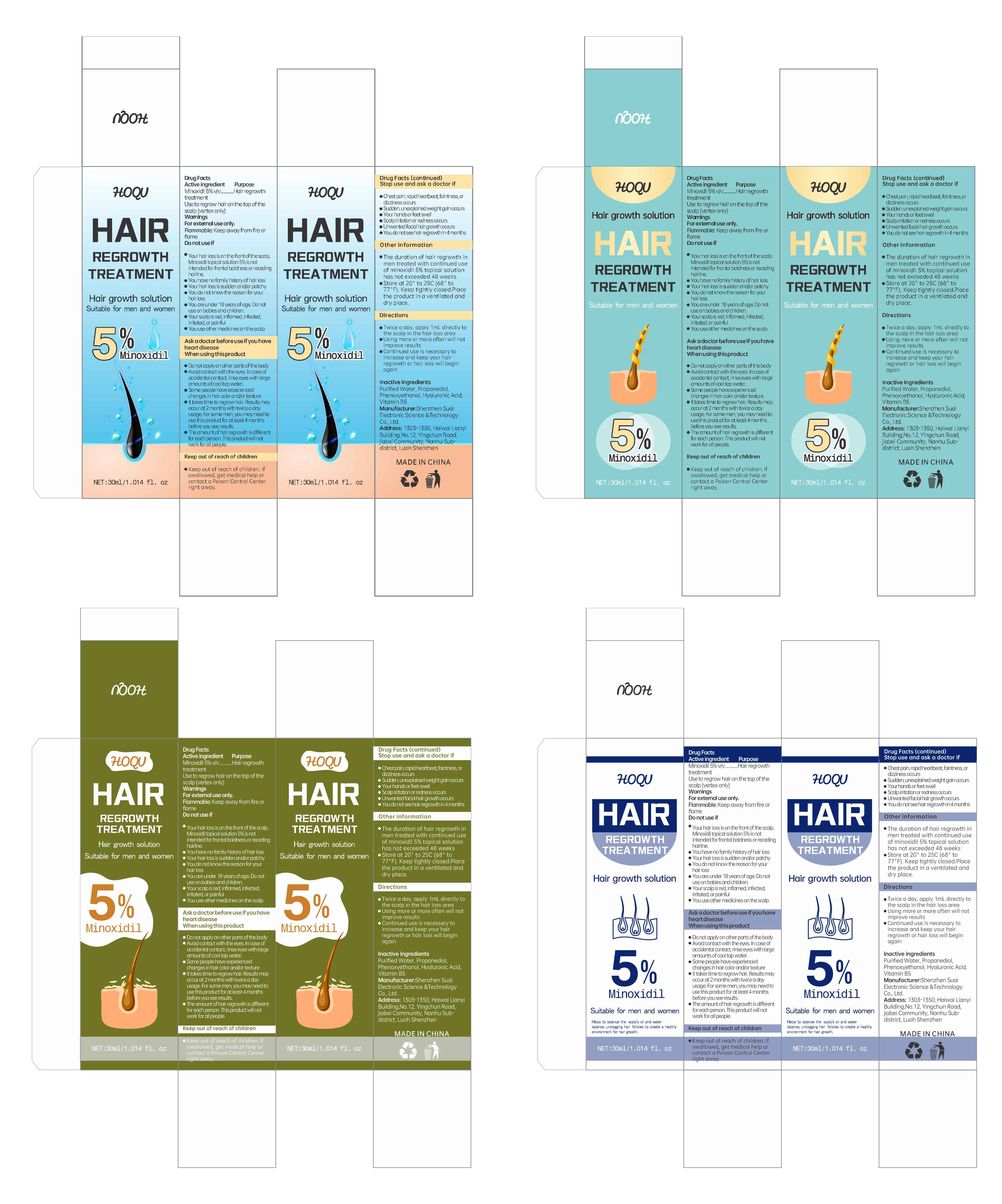 DRUG LABEL: HOQU Hair growth solution
NDC: 84095-005 | Form: LIQUID
Manufacturer: Shenzhen Suai Electronic Science & Technology Co., Ltd.
Category: otc | Type: HUMAN OTC DRUG LABEL
Date: 20240517

ACTIVE INGREDIENTS: MINOXIDIL 5 g/100 mL
INACTIVE INGREDIENTS: PANTOTHENIC ACID; PHENOXYETHANOL; PROPANEDIOL; WATER; HYALURONIC ACID

84095-005

Active Ingredient

Minoxidil 5%

Purpose

Hair regrowth treatment

Use

Use to regrow hair on the top of the scalp (vertex only)

Warnings

For external use only.
Flammable: Keep away from fire or flame

Do not use

1.Your hair loss is on the front of the scalp. Minoxidil topical solution 5% is not intended for frontal baldness or receding hairline.
2.You have no family history of hair loss
3.Your hair loss is sudden and/or patchy
4.You do not know the reason for your hair loss
5.You are under 18 years of age. Do not use on babies and children.
6.Your scalp is red, inflamed, infected, irritated, or painful
7.You use other medicines on the scalp

When Using

1.Do not apply on other parts of the body
2.Avoid contact with the eyes. In case of accidental contact, rinse eyes with large amounts of cool tap water.
3.Some people have experienced changes in hair color and/or texture
4.lt takes time to regrow hair. Results may occur at 2 months with twice a day usage. For some men, you may need to use this product for at least 4 months before you see results.
5.The amount of hair regrowth is different for each person. This product will not work for all people.

Stop Use

1.Chest pain, rapid heartbeat, faintness, or dizziness occurs
2.Sudden, unexplained weight gain occurs
3.Your hands or feet swell
4.Scalp irritation or redness occurs
5.Unwanted facial hair growth occurs
6.You do not see hair regrowth in 4 months

Ask Doctor

1.Chest pain, rapid heartbeat, faintness, or dizziness occurs
2.Sudden, unexplained weight gain occurs
3.Your hands or feet swell
4.Scalp irritation or redness occurs
5.Unwanted facial hair growth occurs
6.You do not see hair regrowth in 4 months

Keep Oot Of Reach Of Children

Keep out of reach of children. lf swallowed, get medical help or contact a Poison Control Center right away.

Directions

1.Twice a day, apply 1mL directly to the scalp in the hair loss area
2.Using more or more often will not improve results
3.Continued use is necessary to increase and keep your hair regrowth or hair loss will begin again

Other information

1.The duration of hair regrowth in men treated with continued use of minoxidil 5% topical solution has not exceeded 48 weeks
2.Store at 20° to 25C (68° to 77°F). Keep tightly closed.Place the product in a ventilated and dry place.

Inactive ingredients

Purified Water, Propanediol, Phenoxyethanol, Hyaluronic Acid, Vitamin B5